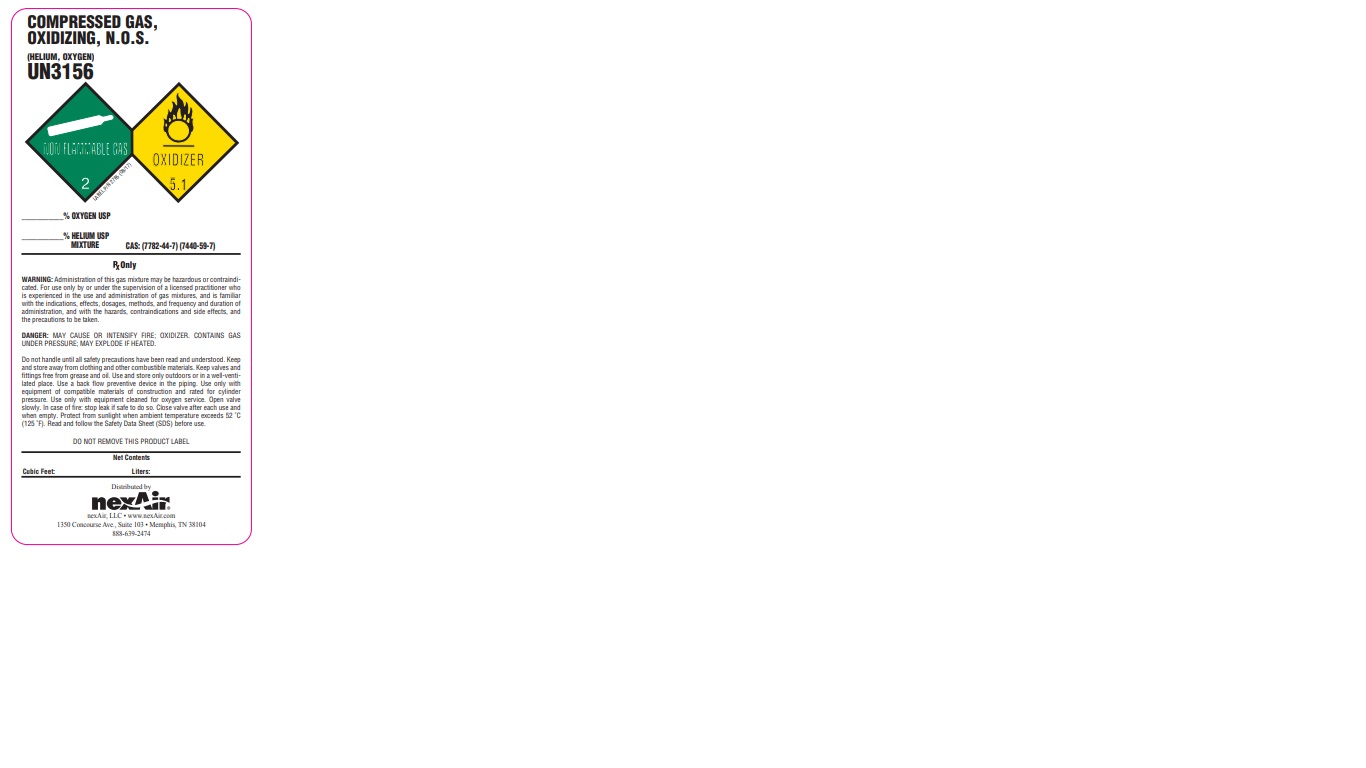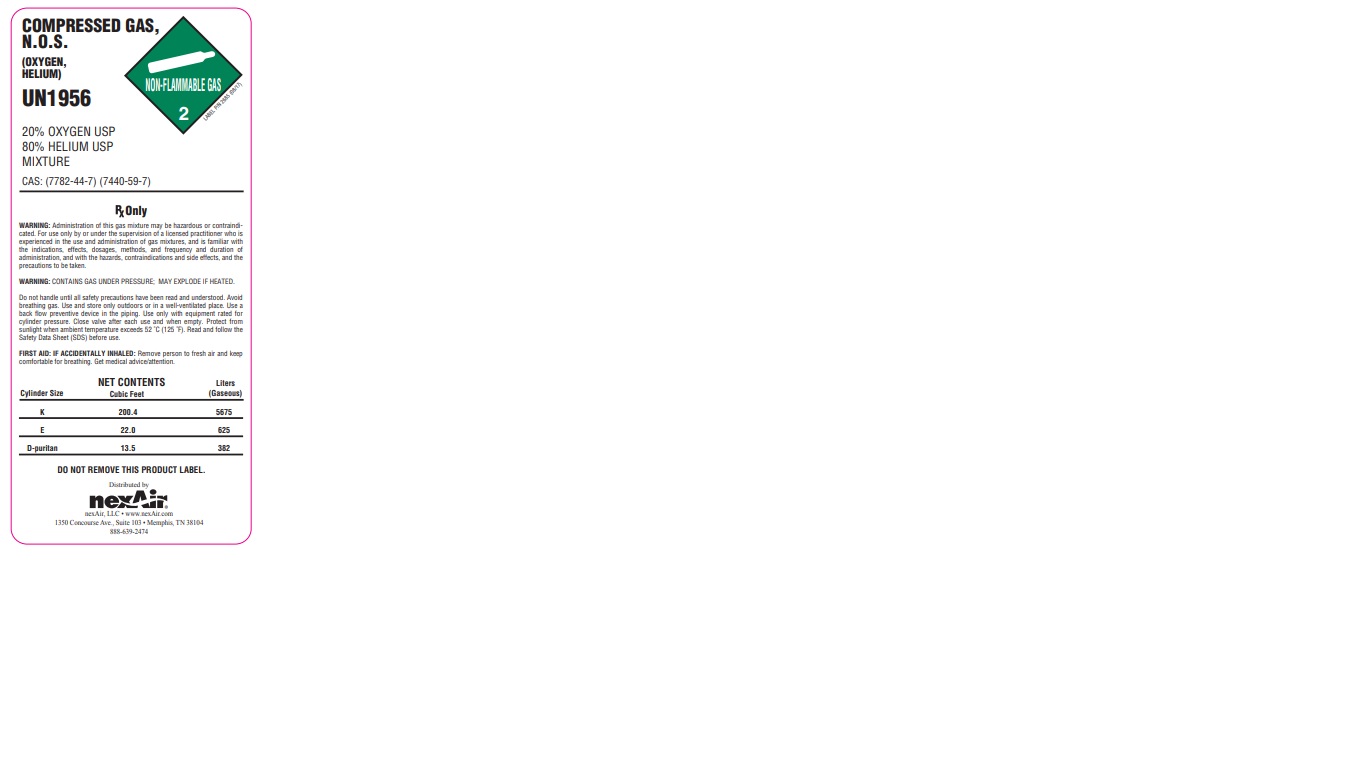 DRUG LABEL: Helium/Oxygen Mix
NDC: 12213-801 | Form: GAS
Manufacturer: NEXAIR, LLC
Category: prescription | Type: HUMAN PRESCRIPTION DRUG LABEL
Date: 20251031

ACTIVE INGREDIENTS: OXYGEN 200 mL/1 L
INACTIVE INGREDIENTS: HELIUM 800 mL/1 L

Helium/oxygen mix

PACKAGE LABEL

COMPRESSED GAS, N.O.S. (OXYGEN, HELIUM)

UN1956

20% OXYGEN USP

80% HELIUM USP

MIXTURE

CAS: (7782-44-7) (7440-59-7)

RX Only

WARNING: Administration of this gas mixture may be hazardous or contraindicated. For use only by or under the supervision of a licensed practitioner who is experienced in the use and administration of gas mixtures, and is familiar with the indications, effects, dosages, methods, and frequency and duration of administration, and with the hazards, contraindications and side effects, and the precautions to be taken.

WARNING: CONTAINS GAS UNDER PRESSURE; MAY EXPLODE IF HEATED.

Do not handle until all safety precautions have been read and understood. Avoid breathing gas. Use and store only outdoors or in well-ventilated place. Use a back flow preventive device in the piping. Use only with equipment rated for cylinder pressure. Close valve after each use and when empty. Protect from sunlight when ambient temperature exceeds 52 C (125 F). Read and follow the Safety Data Sheet (SDS) before use.

FIRST AID: IF ACCIDENTALLY INHALED: Remove person to fresh air and keep comfortable for breathing. Get medical advice/attention.

NET CONTENTS

Cylinder Size Cubic Feet Liters (Gaseous)

K 200.4 5675

E 22.0 625

D-puritan 13.5 382

DO NOT REMOVE THIS PRODICT LABEL.

Distributed by nexAir

nexAir, LLC www.nexAir.com

1350 Concourse Ave., Suite 103 Memphis, TN 38104

888-639-2474

PACKAGE LABEL

COMPRESSED GAS, OXIDIZING, N.O.S. (HELIUM, OXYGEN)

UN3156

% OXYGEN USP

% HELIUM USP MIXTURE CAS: (7782-44-7) (7440-59-7)

RX Only.

WARNING: Administration of this gas mixture may be hazardous or contraindicated. For use only by or under the supervision of a licensed practitioner who is experienced in the use and administration of gas mixtures, and is familiar with the indications, effects, dosages, methods, and frequency and duration of administration, and with the hazards, contraindications and side effects, and the precautions to be taken.

DANGER: MAY CAUSE OR INTENSIFY FIRE; OXIDIZER. CONTAINS GAS UNDER PRESSURE; MAY EXPLODE IF HEATED.

Do not handle until all safety precautions have been read and understood. Keep and store away from clothing and other combustible materials. Keep valves and fittings free from grease and oil. Use and store only outdoors or in well-ventilated place. Use a back flow preventive device in the piping. Use only with equipment rated for oxygen service. Open valve slowly. In case of fire: stop leak if safe to do so. Close valve after each use and when empty. Protect from sunlight when ambient temperature exceeds 52 C (125 F). Read and follow the Safety Data Sheet (SDS) before use.

DO NOT REMOVE THIS PRODICT LABEL.

Net Contents

Cubic Feet Liters

Distributed by nexAir

nexAir, LLC www.nexAir.com

1350 Concourse Ave., Suite 103 Memphis, TN 38104

888-639-2474